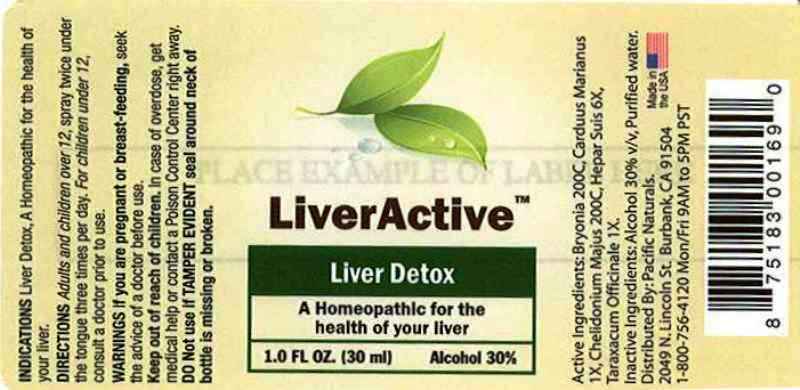 DRUG LABEL: LiverActive
NDC: 50845-0172 | Form: SPRAY
Manufacturer: Liddell Laboratories, Inc.
Category: homeopathic | Type: HUMAN OTC DRUG LABEL
Date: 20120106

ACTIVE INGREDIENTS: BRYONIA ALBA ROOT 200 [hp_C]/1 mL; SILYBUM MARIANUM SEED 1 [hp_X]/1 mL; CHELIDONIUM MAJUS 200 [hp_C]/1 mL; PORK LIVER 6 [hp_X]/1 mL; TARAXACUM OFFICINALE 1 [hp_X]/1 mL
INACTIVE INGREDIENTS: WATER; ALCOHOL

LiverActive

ACTIVE INGREDIENT

ACTIVE INGREDIENTS: Bryonia 200C, Carduus marianus 1X, Chelidonium majus 200C, Hepar suis 6X, Taraxacum officinale 1X.

PURPOSE

INDICATIONS: Liver Detox. A Homeopathic for the health of your liver.

WARNINGS

WARNINGS: If you are pregnant or breast-feeding, seek the advice of a doctor before use.

Keep out of reach of children. In case of overdose, get medical help or contact a Poison Control Center right away.

Do not use if TAMPER EVIDENT seal around neck of bottle is missing or broken.

DOSAGE AND ADMINISTRATION

DIRECTIONS: Adults and children over 12, spray twice under the tongue three times per day. For children under 12, consult a doctor prior to use.

INACTIVE INGREDIENTS: Alcohol 30% v/v, Purified water.

KEEP OUT OF REACH OF CHILDREN. In case of overdose, get medical help or contact a Poison Control Center right away.

INDICATIONS AND USAGE

INDICATIONS: Liver Detox. A Homeopathic for the health of your liver.

QUESTIONS

Distributed by:

Pacific Naturals.

2049 N. Lincoln St.

Burbank, CA 91507

1-800-756-4120 Mon/Fri 9AM to 5PM PST

PACKAGE LABEL

LiverActive

Liver Detox

A Homeopathic for the health of your liver

1.0 fl oz. (30 ml)